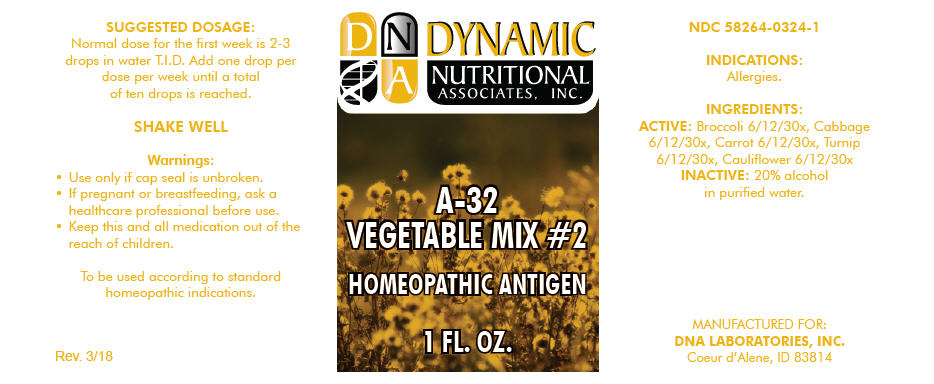 DRUG LABEL: A-32
NDC: 58264-0324 | Form: SOLUTION
Manufacturer: DNA Labs, Inc.
Category: homeopathic | Type: HUMAN OTC DRUG LABEL
Date: 20250109

ACTIVE INGREDIENTS: BROCCOLI 30 [hp_X]/1 mL; CABBAGE 30 [hp_X]/1 mL; CARROT 30 [hp_X]/1 mL; TURNIP 30 [hp_X]/1 mL; CAULIFLOWER 30 [hp_X]/1 mL
INACTIVE INGREDIENTS: ALCOHOL; WATER

A-32

NDC 58264-0324-1

INDICATIONS

PURPOSE

Allergies.

INGREDIENTS

ACTIVE

Broccoli 6/12/30x, Cabbage 6/12/30x, Carrot 6/12/30x, Turnip 6/12/30x, Cauliflower 6/12/30x

INACTIVE

20% alcohol in purified water.

SUGGESTED DOSAGE

Normal dose for the first week is 2-3 drops in water T.I.D. Add one drop per dose per week until a total of ten drops is reached.

STORAGE AND HANDLING

SHAKE WELL

Warnings

- Use only if cap seal is unbroken.

PREGNANCY OR BREAST FEEDING

- If pregnant or breastfeeding, ask a healthcare professional before use.

KEEP OUT OF REACH OF CHILDREN

- Keep this and all medication out of the reach of children.

To be used according to standard homeopathic indications.

PRINCIPAL DISPLAY PANEL - 1 FL. OZ. Bottle Label

DYNAMIC
NUTRITIONAL
ASSOCIATES, INC.

A-32
VEGETABLE MIX #2

HOMEOPATHIC ANTIGEN

1 FL. OZ.